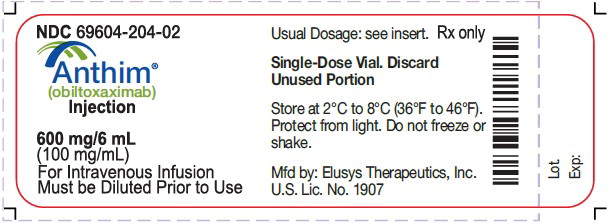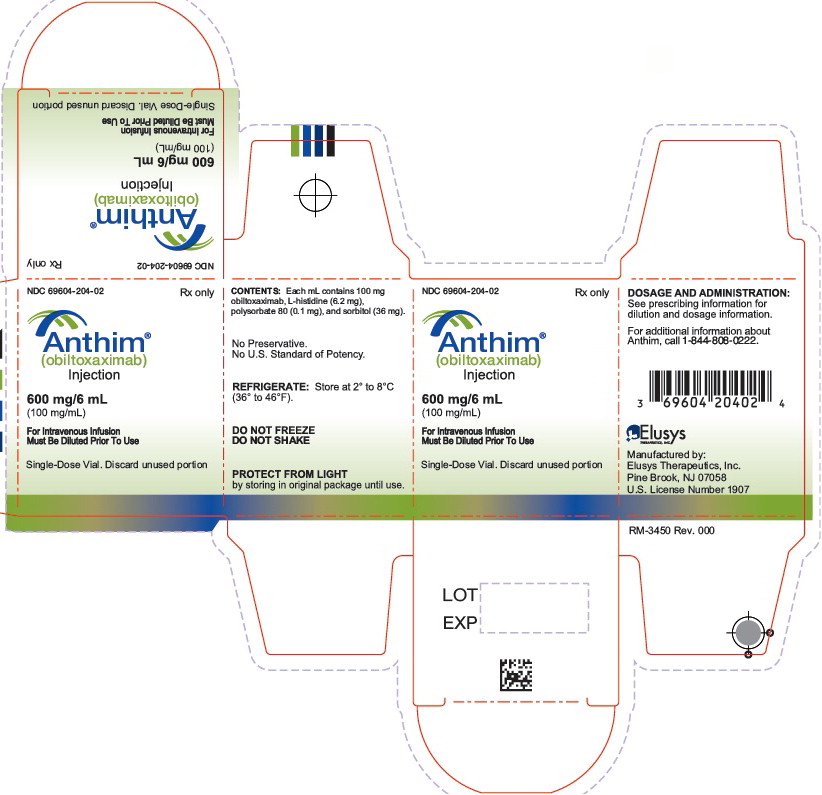 DRUG LABEL: Anthim
NDC: 69604-204 | Form: SOLUTION
Manufacturer: Elusys Therapeutics, Inc.
Category: prescription | Type: HUMAN PRESCRIPTION DRUG LABEL
Date: 20251117

ACTIVE INGREDIENTS: OBILTOXAXIMAB 100 mg/1 mL

HIGHLIGHTS OF PRESCRIBING INFORMATION

These highlights do not include all the information needed to use ANTHIM safely and effectively. See full prescribing information for ANTHIM.
ANTHIM® (obiltoxaximab) injection, for intravenous use
Initial U.S. Approval: 2016

WARNING: HYPERSENSITIVITY and ANAPHYLAXIS

See full prescribing information for complete boxed warning.

- Hypersensitivity reactions, including anaphylaxis, have been reported during ANTHIM infusion (5.1)
- ANTHIM should be administered in monitored settings by personnel trained and equipped to manage anaphylaxis (1.2, 2.4, 5.1)
- Stop ANTHIM infusion immediately and treat appropriately if hypersensitivity or anaphylaxis occurs (2.4, 5.1)

1 INDICATIONS AND USAGE

ANTHIM® is a monoclonal antibody directed against the protective antigen of Bacillus anthracis. It is indicated in adult and pediatric patients for treatment of inhalational anthrax due to B. anthracis in combination with appropriate antibacterial drugs and, for prophylaxis of inhalational anthrax when alternative therapies are not available or are not appropriate. (1.1)

Limitations of Use

- ANTHIM should only be used for prophylaxis when its benefit for prevention of inhalational anthrax outweighs the risk of hypersensitivity and anaphylaxis. (1.2, 5.1)
- The effectiveness of ANTHIM is based solely on efficacy studies in animal models of inhalational anthrax. (1.2, 14)
- There have been no studies of the safety or pharmacokinetics (PK) of ANTHIM in the pediatric population. Dosing in pediatric patients was derived using a population PK approach. (1.2, 8.4)
- ANTHIM does not have direct antibacterial activity. ANTHIM should be used in combination with appropriate antibacterial drugs. (1.2)
- ANTHIM is not expected to cross the blood-brain barrier and does not prevent or treat meningitis. (1.2)

2 DOSAGE AND ADMINISTRATION

- Pre-medicate with diphenhydramine. (2.1, 5.1)
- Recommended Dosage of ANTHIM:
  - Adult Patients: 16 mg/kg. (2.1)
  - Pediatric Patients: (2.2)
    ➢ Greater than 40 kg: 16 mg/kg
    ➢ Greater than 15 kg to 40 kg: 24 mg/kg
    ➢ Less than or equal to 15 kg: 32 mg/kg
- Dilute the injection in 0.9% Sodium Chloride Injection, USP, before administering as an intravenous (IV) infusion over 1 hour and 30 minutes. (2.3)
- Administer ANTHIM in a monitored setting equipped to manage anaphylaxis. (2.4, 5.1)
- See Full Prescribing Information for instructions on preparation, dilution and administration of ANTHIM injection. (2.3, 2.4)

3 DOSAGE FORMS AND STRENGTHS

Injection: 600 mg/6 mL (100 mg/mL) solution in single-dose vial. (3)

4 CONTRAINDICATIONS

None (4)

5 WARNINGS AND PRECAUTIONS

Hypersensitivity reactions, including anaphylaxis (Boxed Warning, 1.2, 2.1, 12.4, 5.1)

6 ADVERSE REACTIONS

Most frequently reported adverse reactions in healthy adult subjects (≥1.5%) were headache, pruritus, infections of the upper respiratory tract, cough, vessel puncture site bruise, infusion site swelling, nasal congestion, infusion site pain, urticaria and pain in extremity. (6.1)

To report SUSPECTED ADVERSE REACTIONS, contact Elusys Therapeutics, Inc. at 1-844-808-0222 or FDA at 1-800-FDA-1088 or www.fda.gov/medwatch.

8 USE IN SPECIFIC POPULATIONS

Pediatric Use: There have been no studies of the safety or PK of ANTHIM in the pediatric population. (1.2, 8.4)

FULL PRESCRIBING INFORMATION

WARNING: HYPERSENSITIVITY and ANAPHYLAXIS

Hypersensitivity and anaphylaxis have been reported during the intravenous infusion of ANTHIM. Due to the risk of hypersensitivity and anaphylaxis, ANTHIM should be administered in monitored settings by personnel trained and equipped to manage anaphylaxis. Monitor individuals who receive ANTHIM closely for signs and symptoms of hypersensitivity reactions throughout the infusion and for a period of time after administration. Stop ANTHIM infusion immediately and treat appropriately if hypersensitivity or anaphylaxis occurs [see Indications and Usage (1.2), Dosage and Administration (2.4) and Warnings and Precautions (5.1)].

1 INDICATIONS AND USAGE

1.1 Inhalational Anthrax

ANTHIM is indicated in adult and pediatric patients for the treatment of inhalational anthrax due to Bacillus anthracis in combination with appropriate antibacterial drugs.

ANTHIM is indicated for prophylaxis of inhalational anthrax due to B. anthracis when alternative therapies are not available or not appropriate [see Indications and Usage (1.2)].

1.2 Limitations of Use

ANTHIM should only be used for prophylaxis when its benefit for prevention of inhalational anthrax outweighs the risk of hypersensitivity and anaphylaxis [see Warnings and Precautions (5.1)].

The effectiveness of ANTHIM is based solely on efficacy studies in animal models of inhalational anthrax. It is not ethical or feasible to conduct controlled clinical trials with intentional exposure of humans to anthrax [see Clinical Studies (14)].

Safety and PK of ANTHIM have been studied in adult healthy volunteers. There have been no studies of safety or PK of ANTHIM in the pediatric population. A population PK approach was used to derive intravenous infusion dosing regimens that are predicted to provide pediatric patients with exposure comparable to the observed exposure in adults [see Use in Specific Populations (8.4)].

ANTHIM binds to the protective antigen (PA) component of B. anthracis toxin; it does not have direct antibacterial activity. ANTHIM is not expected to cross the blood-brain barrier and does not prevent or treat meningitis. ANTHIM should be used in combination with appropriate antibacterial drugs.

2 DOSAGE AND ADMINISTRATION

2.1 Dosage for Adult Patients

- Pre-medicate with diphenhydramine prior to administering ANTHIM [see Warnings and Precautions (5.1)].
- Dilute the injection in 0.9% Sodium Chloride Injection, USP, before administering as an intravenous infusion [see Dosage and Administration (2.3)].
- The recommended dosage of ANTHIM in adult patients is a single dose of 16 mg/kg administered intravenously over 90 minutes (1 hour and 30 minutes) [see Dosage and Administration (2.4)].
- For adult patients weighing less than 40 kg, see Table 1 below.

2.2 Dosage for Pediatric Patients

- Pre-medicate with diphenhydramine prior to administering ANTHIM [see Warnings and Precautions (5.1)].
- Dilute the injection in 0.9% Sodium Chloride Injection, USP, before administering as an intravenous infusion [see Dosage and Administration (2.3)].
- The recommended dose for pediatric patients is based on weight as shown in Table 1 below.

Table 1. Recommended Pediatric Dose of ANTHIM (weight-based dosing)
Body Weight | Dose
Greater than 40 kg | 16 mg/kg
Greater than 15 kg to 40 kg | 24 mg/kg
Less than or equal to 15 kg | 32 mg/kg

- Administer the recommended dose of ANTHIM intravenously over 90 minutes (1 hour and 30 minutes) [see Dosage and Administration (2.4)].

There have been no studies of the safety or PK of ANTHIM conducted in the pediatric population. The dosing recommendations in Table 1 are derived from simulations using a population PK approach designed to match the observed adult exposure to ANTHIM at a 16 mg/kg dose [see Use in Specific Populations (8.4)].

2.3 Preparation and Dilution for Administration

Important Preparation Instructions

- Keep vials in their cartons prior to preparation of an infusion solution to protect ANTHIM from light. ANTHIM vials contain no preservative.
- Parenteral drug products should be inspected visually for particulate matter and discoloration prior to administration, whenever solution and container permit.
- Discard the vial if the solution is discolored or contains extraneous particles other than a few translucent-to- white, proteinaceous particles [see Description (11)].
- Do not shake the vial.

Table 2. ANTHIM Dose, Total Infusion Volume and Infusion Rate by Body Weight
Body Weight (weight-based dosing) | Total Infusion Volume | Infusion Rate
Greater than 40 kg or adult (16 mg/kg)
Greater than 40 kg | 250 mL | 167 mL/hr
Greater than 15 kg to 40 kg (24 mg/kg)
31 kg to 40 kg | 250 mL | 167 mL/hr
16 kg to 30 kg | 100 mL | 67 mL/hr
15 kg or less (32 mg/kg)
11 kg to 15 kg | 100 mL | 67 mL/hr
5 kg to 10 kg | 50 mL | 33.3 mL/hr
3.1 kg to 4.9 kg | 25 mL | 17 mL/hr
2.1 kg to 3 kg | 20 mL | 13.3 mL/hr
1.1 kg to 2 kg | 15 mL | 10 mL/hr
1 kg or less | 7 mL | 4.7 mL/hr

Preparation and Dilution in Bag for Infusion

1. Calculate the milligrams of ANTHIM injection needed by multiplying the recommended mg/kg dose in Table 2 by the patient weight in kilograms.
2. Calculate the required volume in milliliters of ANTHIM injection and number of vials needed for the dose by dividing the calculated dose in milligrams (step 1) by the concentration, 100 mg/mL. Each single vial allows delivery of 6 mL of ANTHIM.
3. Select an appropriate size bag of 0.9% Sodium Chloride Injection, USP. Withdraw a volume of solution from the bag equal to the calculated volume in milliliters of ANTHIM in step 2 above. Discard the solution that was withdrawn from the bag.
4. Withdraw the required volume of ANTHIM injection (calculated from step 2) from the ANTHIM vial(s). Discard any unused portion remaining in the ANTHIM vial(s).
5. Transfer the required volume of ANTHIM injection to the selected infusion bag.
6. Gently invert the bag to mix the solution. Do not shake.
7. The prepared solution is stable for 8 hours stored at room temperature 20°C to 25°C (68°F to 77°F) or 8 hours stored in the refrigerator at 2°C to 8°C (36°F to 46°F).

Preparation and Dilution in Syringe for Infusion

- Calculate lunused product.

2.4 Administration

- Administer ANTHIM in appropriately monitored settings which are equipped to manage anaphylaxis [see Warnings and Precautions (5.1)].
- Dilute ANTHIM injection [see Dosage and Administration (2.3)] before administering ANTHIM intravenously using the bag or syringe for infusion.
- After preparation of the bag or syringe for infusion administer the infusion solution using a 0.22 micron inline filter with the infusion rate described in Table 2 [see Dosage and Administration (2.3)].
- Administer diluted ANTHIM intravenous infusion over 1 hour and 30 minutes. Monitor patients closely for signs and symptoms of hypersensitivity throughout the infusion and for a period of time after administration [see Warnings and Precautions (5.1)].
- Stop the infusion immediately and treat appropriately, if hypersensitivity or anaphylaxis occurs [see Warnings and Precautions (5.1)].
- Flush the line with 0.9% Sodium Chloride Injection, USP at the end of the intravenous infusion.

3 DOSAGE FORMS AND STRENGTHS

Injection: 600 mg/6 mL (100 mg/mL) in a single-dose vial.

ANTHIM is a clear to opalescent, colorless to pale yellow to pale brownish-yellow solution and may contain few translucent-to-white proteinaceous particulates.

4 CONTRAINDICATIONS

None.

5 WARNINGS AND PRECAUTIONS

5.1 Hypersensitivity and Anaphylaxis

Hypersensitivity reactions were the most common adverse reactions in the safety trials of ANTHIM, occurring in 34/320 healthy subjects (10.6%). Three (0.9%) cases of anaphylaxis occurred during or immediately after the infusion. In clinical trials, manifestations of anaphylaxis were rash/urticaria, cough, dyspnea, cyanosis, postural dizziness and chest discomfort. ANTHIM infusion was discontinued in 8 (2.5%) subjects due to hypersensitivity or anaphylaxis. The adverse reactions reported in these 8 subjects included urticaria, rash, cough, pruritus, dizziness, throat irritation, dysphonia, dyspnea and chest discomfort. The remaining subjects with hypersensitivity had predominantly skin-related symptoms such as pruritus and rash, and 6 subjects reported cough [see Adverse Reactions 6.1].

Due to the risk of anaphylaxis, ANTHIM should be administered in monitored settings by personnel trained and equipped to manage anaphylaxis. Patients should be monitored closely throughout the infusion period and for a period of time after administration [see Patient Counseling Information (17)]. If anaphylaxis or hypersensitivity reactions occur, stop the infusion immediately and treat appropriately.

Premedication with diphenhydramine is recommended prior to administration of ANTHIM [see Dosage and Administration (2.1) and Adverse Reactions (6.1)]. Diphenhydramine premedication does not prevent anaphylaxis, and may mask or delay onset of symptoms of hypersensitivity.

6 ADVERSE REACTIONS

The following clinically important adverse reactions are described elsewhere in the labeling:

- Hypersensitivity and Anaphylaxis [see Warnings and Precautions (5.1)].

6.1 Clinical Trials Experience

Because clinical trials are conducted under widely varying conditions, adverse reaction rates observed in the clinical trials of a drug cannot be directly compared to rates in the clinical trials of another drug and may not reflect the rates observed in practice. The safety of ANTHIM has been studied only in healthy volunteers. It has not been studied in patients with inhalational anthrax.

The safety of ANTHIM was evaluated in 320 healthy subjects treated with one or more 16 mg/kg IV doses in three clinical studies. Study 1 was a placebo-controlled study evaluating a single dose of ANTHIM vs. placebo (210 subjects received ANTHIM, 70 received placebo). Study 2 was a repeat-dose study in which 70 subjects received the first dose, but 34 and 31 subjects received a second dose of ANTHIM in sequences A (2 weeks apart) and B (≥ 4 months apart), respectively. Study 3 was a drug interaction study of a single dose of ANTHIM with ciprofloxacin in 40 subjects (20 subjects received ANTHIM alone and 20 subjects received ANTHIM plus ciprofloxacin for 9 days).

Subjects were 18 to 79 years of age, 54% were male, 70% Caucasian, 26% Black/African American, 2% American Indian/Alaska Native, 1% Asian and 10% Hispanic.

Adverse Reactions Leading to Discontinuation of ANTHIM Infusion

ANTHIM infusion was discontinued in 8/320 healthy subjects (2.5%) in clinical trials due to hypersensitivity reactions or anaphylaxis [see Warnings and Precautions (5.1)].

Most Frequently Reported Adverse Reactions

The most frequently reported adverse reactions were headache, pruritus, infections of the upper respiratory tract, cough, vessel puncture site bruise, infusion site swelling, urticaria, nasal congestion, infusion site pain, and pain in extremity.

Table 3 shows the adverse reactions that occurred in ≥1.5% of healthy subjects receiving a single dose of ANTHIM (16 mg/kg IV) and more frequently than those receiving placebo.

Table 3. Adverse Reactions Reported in ≥1.5% of Healthy Adult Subjects Exposed to a Single Dose of ANTHIM 16 mg/kg IV
Adverse Reactions | Placebo N = 70 (%) | Single Dose ANTHIM N = 300* (%)
Headache | 4 (6%) | 24 (8%)
Pruritus | 1 (1%) | 11 (4%)
Infections of the upper respiratory tract | 2 (3%) | 14 (5%)
Cough | 0 | 9 (3%)
Vessel puncture site bruise | 1 (1%) | 8 (3%)
Infusion site swelling | 1 (1%) | 8 (3%)
Nasal congestion | 1 (1%) | 5 (2%)
Infusion site pain | 0 | 7 (2%)
Urticaria | 0 | 5 (2%)
Pain in extremity | 1 (1%) | 5 (2%)
*Single-dose population: 210 subjects in study 1 plus 70 subjects in the first treatment period of study 2 plus 20 subjects in the ANTHIM alone treatment arm of study 3

Effect of Diphenhydramine on the Incidence of Adverse Reactions

Overall in the single-dose population, subjects who received pre-medication with diphenhydramine were less likely to experience adverse reactions with administration of ANTHIM compared to those who did not (42% vs. 58% respectively). Specifically, the incidence of the following adverse reactions was lower in the subjects who received diphenhydramine prior to ANTHIM infusion compared to those who did not: headache (5% vs. 16%), cough (1% vs. 8%), rash (2% vs. 7%), pruritus (3% vs. 4%) throat irritation (0 vs. 3%), rhinorrhea (0 vs. 3%), and infusion site erythema (0% vs. 4%). Somnolence was only reported in subjects who were pretreated with diphenhydramine.

Less Common Adverse Reactions

Clinically important adverse reactions that were reported in <1.5% of subjects exposed to ANTHIM and at rates higher than in placebo subjects are listed below:

- General disorders and administration site conditions: chest discomfort/pain, fatigue, pyrexia, intravenous site discoloration
- Musculoskeletal and connective tissue disorders: myalgia, musculoskeletal pain
- Respiratory, thoracic and mediastinal disorders: oropharyngeal pain, sinus congestion, rhinorrhea, dysphonia, dyspnea
- Investigations: lymphocyte count decreased, neutrophil count decreased, white blood count decreased, increased creatine phosphokinase
- Cardiac disorders: palpitations, cyanosis
- Neurologic disorders: dizziness
- Gastrointestinal disorders: vomiting, dry mouth

6.2 Immunogenicity

As with all therapeutic proteins, there is a potential for immunogenicity. The development of anti-ANTHIM antibodies was evaluated in all subjects receiving single and double doses of ANTHIM in studies 1, 2 and 3. Eight subjects (2.5%) who received at least one dose of IV ANTHIM were positive for a treatment-emergent anti-therapeutic antibody (ATA) response. Quantitative titers were low ranging from 1:20 – 1:320. There was no evidence of altered PK or toxicity profile in subjects with ATA development.

The incidence of antibody formation is highly dependent on the sensitivity and specificity of the immunogenicity assay. Additionally, the observed incidence of any antibody positivity in an assay is highly dependent on several factors, including assay sensitivity and specificity, assay methodology, sample handling, timing of sample collection, concomitant medications, and underlying disease. For these reasons, comparison of incidence of antibodies to obiltoxaximab with the incidence of antibodies to other products may be misleading.

7 DRUG INTERACTIONS

7.1 Ciprofloxacin

Co-administration of 16 mg/kg ANTHIM intravenously with intravenous or oral ciprofloxacin in human subjects did not alter the PK of either ciprofloxacin or obiltoxaximab [see Clinical Pharmacology (12.3)].

8 USE IN SPECIFIC POPULATIONS

8.1 Pregnancy

Risk Summary

There are no data on the use of ANTHIM in pregnant women to inform on drug-associated risk. There are adverse effects on maternal and fetal outcomes associated with anthrax in pregnancy (see Clinical Considerations). In pregnant rabbits, intravenous administration of obiltoxaximab during organogenesis was not associated with adverse developmental outcomes at up to 0.62 times the human systemic exposure at the maximum recommended adult dose (see Data).

The estimated background risk of major birth defects and miscarriage for the indicated population is unknown. All pregnancies have a background risk of birth defect, loss, or other adverse outcomes. In the U.S. general population, the estimated background risk of major birth defects and miscarriage in clinically recognized pregnancies is 2% to 4% and 15% to 20%, respectively.

Clinical Considerations

Disease-Associated Maternal and/or Embryo/Fetal Risk:

Limited data in the form of case reports of anthrax infection in pregnant women indicate that maternal infection is associated with a high risk of maternal, fetal, and neonatal deaths, particularly in the absence of treatment.

Data

Animal Data:

A study was conducted in pregnant, healthy, New Zealand White rabbits administered intravenous obiltoxaximab at dose levels of 16 or 32 mg/kg during organogenesis on Gestation Days 6, 10, 13 and 17. No maternal toxicity or adverse developmental outcomes were observed at the highest tested dose, 32 mg/kg. In those rabbits, mean maternal maximum plasma concentration (Cmax = 1180 mcg/mL) and mean maternal AUCinf (3220 mcg•day/mL) were approximately 3 times and 0.62 times the respective values for Cmax and AUC reported in clinical trial subjects at the maximum recommended adult dose of 16 mg/kg.

8.2 Lactation

Risk Summary

There is no information available on the presence of obiltoxaximab in human milk, the effects on the breastfed child, or the effects on milk production. Maternal IgG is known to be present in human milk. Therefore, the development and health benefits of breastfeeding should be considered along with the mother's clinical need for ANTHIM and any potential adverse effects on the breastfed child from ANTHIM or from the underlying maternal condition.

8.4 Pediatric Use

As in adults, the effectiveness of ANTHIM in pediatric patients is based solely on efficacy studies in animal models of inhalational anthrax. As exposure of healthy children to ANTHIM is not ethical, a population PK approach was used to derive intravenous dosing regimens that are predicted to provide pediatric patients with exposure comparable to the observed exposure in adults receiving 16 mg/kg. The dose for pediatric patients is based on weight [see Dosage and Administration (2.2)].

There have been no studies of safety or PK of ANTHIM in the pediatric population.

8.5 Geriatric Use

Clinical studies of ANTHIM did not include sufficient numbers of subjects aged 65 years and over to determine whether they respond differently from younger subjects. Of the 320 subjects in clinical studies of ANTHIM, 9.4% (30/320) were 65 years and over, while 2% (6/320) were 75 years and over. No alteration of dosing is needed for patients ≥65 years of age [see Clinical Pharmacology (12.3)].

10 OVERDOSAGE

There is no clinical experience with overdosage of ANTHIM. In case of overdosage, monitor patients for any signs or symptoms of adverse effects.

11 DESCRIPTION

Obiltoxaximab is a chimeric IgG1 kappa monoclonal antibody (mAb) that binds the PA component of B. anthracis toxin. It has an approximate molecular weight of 148 kDa.

ANTHIM injection is a sterile, preservative-free, clear to opalescent, colorless to pale yellow to pale brownish-yellow solution that may contain few translucent-to-white proteinaceous particulates. ANTHIM is supplied as 600 mg/6 mL in single-dose vials for intravenous infusion. Each mL contains 100 mg obiltoxaximab in L-histidine (6.2 mg), polysorbate 80 (0.1 mg), sorbitol (36 mg) with a pH of 5.5.

12 CLINICAL PHARMACOLOGY

12.1 Mechanism of Action

Obiltoxaximab is a monoclonal antibody that binds the PA of B. anthracis [see Microbiology (12.4)].

12.3 Pharmacokinetics

The PK of obiltoxaximab are linear over the dose range of 4 mg/kg (0.25 times the lowest recommended dose) to 16 mg/kg following single IV administration in healthy subjects. Following single IV administration of ANTHIM 16 mg/kg in healthy, male and female human subjects, the mean Cmax and AUCinf were 400 ± 91.2 mcg/mL and 5170 ± 1360 mcg•day/mL, respectively.

Repeat Dosing

Although ANTHIM is intended for single dose administration, the PK of obiltoxaximab following a second dose administration of 16 mg/kg IV given 2 weeks or ≥ 4 months after the first 16 mg/kg IV dose was assessed in 65 healthy subjects (study 2). The obiltoxaximab AUCinf following two 16 mg/kg doses 2 weeks apart was approximately twice that after a single 16 mg/kg dose on Day 1 or Day 120. No significant differences in mean estimates of Cmax, AUCinf, CL, or half-life of obiltoxaximab between the 2 doses administered ≥4 months apart were observed.

Distribution

Mean obiltoxaximab steady-state volume of distribution was greater than plasma volume, suggesting some tissue distribution.

Elimination

Clearance values were much smaller than the glomerular filtration rate, indicating that there is virtually no renal clearance of obiltoxaximab.

Because the effectiveness of ANTHIM cannot be evaluated in humans, a comparison of ANTHIM exposures achieved in healthy human subjects to those observed in animal models of inhalational anthrax in therapeutic efficacy studies is necessary to support the dosage regimen of 16 mg/kg IV as a single dose for the treatment of inhalational anthrax in humans. Based on observed and simulated data, humans achieve similar obiltoxaximab Cmax and greater AUCinf following a single 16 mg/kg IV dose compared to exposures achieved in NZW rabbits and cynomolgus macaques.

Specific Populations

Gender, Age, and Race

ANTHIM PK were evaluated via a population PK analysis using serum samples from 303 healthy adult subjects who received a single IV dose across 3 clinical trials. Based on this analysis, gender (female versus male), race (non-Caucasian versus Caucasian), or age (elderly versus young) had no meaningful effects on the PK parameters for ANTHIM.

Pediatric Population

ANTHIM PK have not been evaluated in children [see Dosage and Administration (2.2) and Use in Specific Populations (8.4)].

Drug Interaction Studies

Ciprofloxacin

In an open-label study evaluating the effect of ciprofloxacin on obiltoxaximab PK in healthy adult male and female subjects (study 3), the administration of 16 mg/kg ANTHIM IV infusion prior to ciprofloxacin IV infusion or ciprofloxacin oral tablets twice daily did not alter the PK of obiltoxaximab. Likewise, obiltoxaximab did not alter the PK of ciprofloxacin administered orally and/or intravenously [see Drug Interactions (7.1)].

12.4 Microbiology

Mechanism of Action

Obiltoxaximab is a monoclonal antibody that binds free PA with an affinity equilibrium dissociation constant (Kd) of 0.33 nM. Obiltoxaximab inhibits the binding of PA to its cellular receptors, preventing the intracellular entry of the anthrax lethal factor and edema factor, the enzymatic toxin components responsible for the pathogenic effects of anthrax toxin.

Activity In Vitro and In Vivo

Obiltoxaximab binds in vitro to PA from the Ames, Vollum, and Sterne strains of B. anthracis. Obiltoxaximab binds to an epitope on PA that is conserved across reported strains of B. anthracis.

In vitro studies in a cell-based assay, using murine macrophages, suggest that obiltoxaximab neutralizes the toxic effects of lethal toxin, a combination of PA + lethal factor.

In vivo efficacy studies in NZW rabbits and cynomolgus macaques challenged with the spores of the Ames strain of B. anthracis by the inhalational route, showed a dose-dependent increase in survival following treatment with ANTHIM. Exposure to B. anthracis spores resulted in increasing concentrations of PA in the serum of NZW rabbits and cynomolgus macaques. After treatment with ANTHIM there was a decrease in PA concentrations in a majority of surviving animals. PA concentrations in placebo animals increased until they died [see Clinical Studies (14)].

13 NONCLINICAL TOXICOLOGY

13.1 Carcinogenesis, Mutagenesis, Impairment of Fertility

Carcinogenicity, genotoxicity, and fertility studies have not been conducted with obiltoxaximab.

13.2 Animal Toxicology and/or Pharmacology

Central nervous system (CNS) lesions (bacteria, inflammation, hemorrhage and occasionally necrosis) were seen in anthrax-infected non-surviving NZW rabbits and cynomolgus macaques administered IV obiltoxaximab (≥4 mg/kg) or control at the time of disease confirmation. Microscopic changes in the non-surviving animals that received obiltoxaximab were due to the presence of extravascular bacteria and not the effect of obiltoxaximab. No dose response relationship for brain histopathology was identified. No treatment-related brain lesions were shown in anthrax-infected surviving NZW rabbits (at day 28) or cynomolgus macaques (up to day 56) after a single administration of obiltoxaximab at doses up to 16 mg/kg and up to 32 mg/kg/dose, respectively. No obiltoxaximab-related neurobehavioral effects were observed in surviving anthrax-infected cynomolgus macaques following treatment with obiltoxaximab.

14 CLINICAL STUDIES

Overview

Because it is not feasible or ethical to conduct controlled clinical trials in humans with inhalational anthrax, the efficacy of ANTHIM for the treatment of inhalational anthrax is based on efficacy studies in NZW rabbits and cynomolgus macaques. The animal efficacy studies are conducted under widely varying conditions, such that the survival rates observed in the animal studies cannot be directly compared between studies and may not reflect the rates observed in clinical practice.

Types of Studies

The efficacy of ANTHIM for treatment and prophylaxis of inhalational anthrax was studied in multiple studies in the cynomolgus macaque and NZW rabbit models of inhalational anthrax. These studies tested the efficacy of ANTHIM compared to placebo and the efficacy of ANTHIM in combination with antibacterial drugs relative to the antibacterial drugs alone.

Study Design

The animals were challenged with aerosolized B. anthracis spores (Ames strain) at approximately 200xLD50 to achieve 100% mortality if untreated. In prophylaxis studies of inhalational anthrax, animals were treated prior to the development of symptoms. In treatment studies, animals were administered treatment after exhibiting clinical signs or symptoms of systemic anthrax. Cynomolgus macaques were treated at the time of a positive serum electrochemiluminescence (ECL) assay for B. anthracis PA at a mean time of approximately 40 hours post-challenge with B. anthracis. In NZW rabbit treatment studies, animals were treated after a positive ECL assay for PA or sustained elevation of body temperature above baseline, at a mean time of approximately 30 hours post-challenge; the majority of animals triggered by temperature. In some of the treatment studies assessing the effect of ANTHIM in combination with antibacterial drugs, treatment was delayed to 72 to 96 hours post-challenge. Most study animals were bacteremic and had a positive ECL assay for PA prior to treatment. Survival was assessed at 28 days post-challenge with B. anthracis in most studies.

Results

NZW rabbit studies 1 and 2 and cynomolgus macaque studies 3 and 4 evaluated treatment with ANTHIM 16 mg/kg IV single dose compared to placebo in animals with systemic anthrax. Treatment with ANTHIM alone resulted in statistically significant improvement in survival relative to placebo (Table 4).

Table 4. Survival Proportions in Monotherapy Treatment Studies of 16 mg/kg IV, All Randomized Animals Positive for Bacteremia Prior to Treatment
 | Proportion of Survival at Day 28^1 (# survived/n) |  | p-value^2 | 95% CI^3
 | Placebo | ANTHIM 16 mg/kg IV | p-value^2 | 95% CI^3
NZW Rabbits
Study 1 | 0 (0/9) | 93% (13/14) | 0.0010 | (0.59, 1.00)
Study 2 | 0 (0/13) | 62% (8/13) | 0.0013 | (0.29, 0.86)
Cynomolgus Macaques
Study 3 | 6% (1/16) | 47% (7/15) | 0.0068 | (0.09, 0.68)
Study 4^4 | 0 (0/17) | 31% (5/16) 35% (6/17) | 0.0085 0.0055 | (0.08, 0.59) (0.11, 0.62)
IV: intravenous, CI: Confidence Interval
^1Survival assessed 28 days after spore challenge
^2p-value is from 1-sided Boschloo Test (with Berger-Boos modification of gamma=0.001) compared to placebo
^3Exact 95% confidence interval of difference in survival rates
^4ANTHIM products manufactured at two different facilities were tested in two separate treatment arms

ANTHIM administered in combination with antibacterial drugs (levofloxacin, ciprofloxacin and doxycycline) for the treatment of systemic inhalational anthrax disease resulted in higher survival outcomes than antibacterial therapy alone in multiple studies where ANTHIM and antibacterial therapy was given at various doses and treatment times.

ANTHIM administered as prophylaxis resulted in higher survival outcomes compared to placebo in multiple studies where treatment was given at various doses and treatment times. In one study, cynomolgus macaques were administered ANTHIM 16 mg/kg at 18 hours, 24 hours or 36 hours after exposure. Survival was 6/6 (100%) at 18 hours, 5/6 (83%) at 24 hours, and 3/6 (50%) at 36 hours. Another cynomolgus macaque study evaluated ANTHIM 16 mg/kg administered 72, 48 or 24 hours prior to exposure. Survival was 100% at all three time points (14/14, 14/14, 15/15, respectively) at day 56 (end of study).

16 HOW SUPPLIED/STORAGE AND HANDLING

ANTHIM injection is a sterile, preservative-free, clear to opalescent, colorless to pale yellow to pale brownish-yellow solution that may contain few translucent-to-white proteinaceous particulates in single-dose vials containing 600 mg/6 mL (100 mg/mL) and is available in the following packaging configuration:

Carton: Contains one (1) single-dose vial of ANTHIM 600 mg/6 mL (NDC 69604-204-02).

Store in refrigerator at 2°C to 8°C (36°F to 46°F) in original carton to protect from light. Do Not Freeze. Do Not Shake.

17 PATIENT COUNSELING INFORMATION

Advise the patient to read the FDA-approved patient labeling (Patient Information).

Efficacy Based on Animal Models Alone

Inform patients that:

- The effectiveness of ANTHIM has been studied only in animals with inhalational anthrax. ANTHIM has not been tested in people who have inhalational anthrax.
- The safety of ANTHIM has been studied in healthy adults, but no safety data are available in pediatric patients or pregnant women. Limited data are available in geriatric subjects [see Use in Specific Populations (8.5)].

Hypersensitivity Reactions and Anaphylaxis

Inform patients that hypersensitivity reactions, including anaphylaxis, have occurred with administration of ANTHIM. Inform patients of the signs and symptoms of hypersensitivity reactions and anaphylaxis and instruct patients to seek immediate medical care if they experience such symptoms during or following administration of ANTHIM [see Warnings and Precautions (5.1)].

Manufactured by:

Elusys
THERAPEUITICS, INC

Elusys Therapeutics, Inc.
2001 Route 46, Suite 310
Parsippany, NJ 07054
U.S. License Number 1907

PATIENT INFORMATION
ANTHIM® (an(t)-thim)
obiltoxaximab
injection, for intravenous use

What is the most important information I should know about ANTHIM?
ANTHIM can cause serious side effects, including:

- Serious allergic reactions. Tell your healthcare provider right away if you have itching, hives, rash, throat irritation, cough, dizziness, shortness of breath or chest discomfort while receiving ANTHIM.

What is ANTHIM?

- ANTHIM is a prescription medicine used along with antibiotic medicines to treat people with inhalational anthrax. ANTHIM can also be used to prevent anthrax disease when there are no other treatment options.
- The effectiveness of ANTHIM has been studied only in animals with inhalational anthrax. There have been no studies in people who have inhalational anthrax.
- The safety of ANTHIM was studied in healthy adults. There have been no studies of ANTHIM in children younger than 18 years.
- ANTHIM is not used in prevention or treatment of anthrax meningitis.

Before you receive ANTHIM, tell your healthcare provider about all of your medical conditions, including if you are:

- allergic to obiltoxaximab or any of the ingredients in ANTHIM. See the end of this leaflet for a list of ingredients in ANTHIM.
- allergic to diphenhydramine (Benadryl®)
- pregnant or planning to become pregnant. It is not known if ANTHIM will harm your unborn baby.
- breastfeeding or plan to breastfeed. It is not known if ANTHIM passes into your breast milk. You and your healthcare provider should decide if you will receive ANTHIM or breastfeed.

Tell your healthcare provider about all the medicines you take, including prescription and over-the-counter medicines, vitamins, and herbal supplements.

How will I receive ANTHIM?

- You will be given 1 dose of ANTHIM by a healthcare provider through a vein (IV or intravenous infusion). It takes about 1 hour and 30 minutes to give you the full dose of medicine.
- Your healthcare provider should give you a medicine called diphenhydramine (Benadryl®) before you receive ANTHIM to help reduce your chances of developing a skin reaction from ANTHIM. Benadryl may be given to you to take by mouth or through a vein.
- Benadryl may make you sleepy, and you should use caution if you will be driving or operating equipment.

What are the possible side effects of ANTHIM?
The most common side effects of ANTHIM include headache, itching, upper respiratory tract infections, cough, IV site bruising, swelling and/or pain, stuffy nose (nasal congestion), hives, and pain in the hands or feet.
Tell your healthcare provider if you have any side effect that bothers you or that does not go away. These are not all the possible side effects of ANTHIM. For more information, ask your healthcare provider.
Call your doctor for medical advice about side effects. You may report side effects to FDA at 1-800-FDA-1088. For more information go to dailymed.nlm.nih.gov.

General information about the safe and effective use of ANTHIM.

- This patient information leaflet summarizes the most important information about ANTHIM. If you would like more information, talk to your healthcare provider. You can ask your pharmacist or healthcare provider for information about ANTHIM that is written for health professionals.

What are the ingredients in ANTHIM?
Active ingredient: Obiltoxaximab
Inactive ingredients: L-histidine, sorbitol and polysorbate 80
Manufactured by: Elusys Therapeutics, Inc., Parsippany, NJ 07054, U.S. License Number 1907
For more information call 1-844-808-0222

The Patient Information has been approved by the U.S. Food and Drug Administration

06/2023